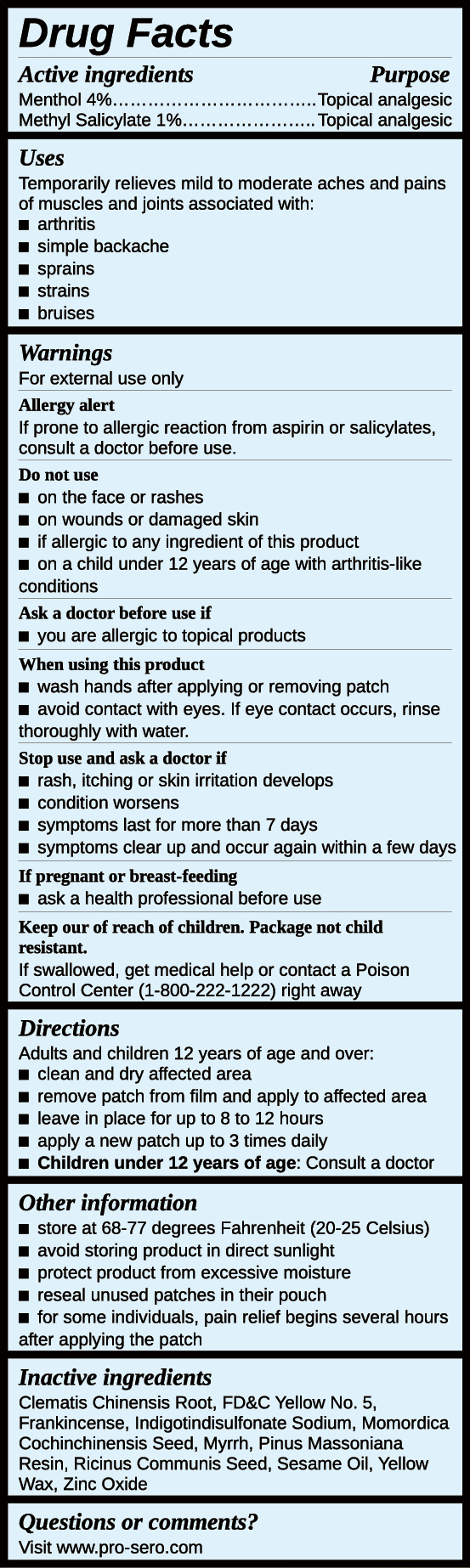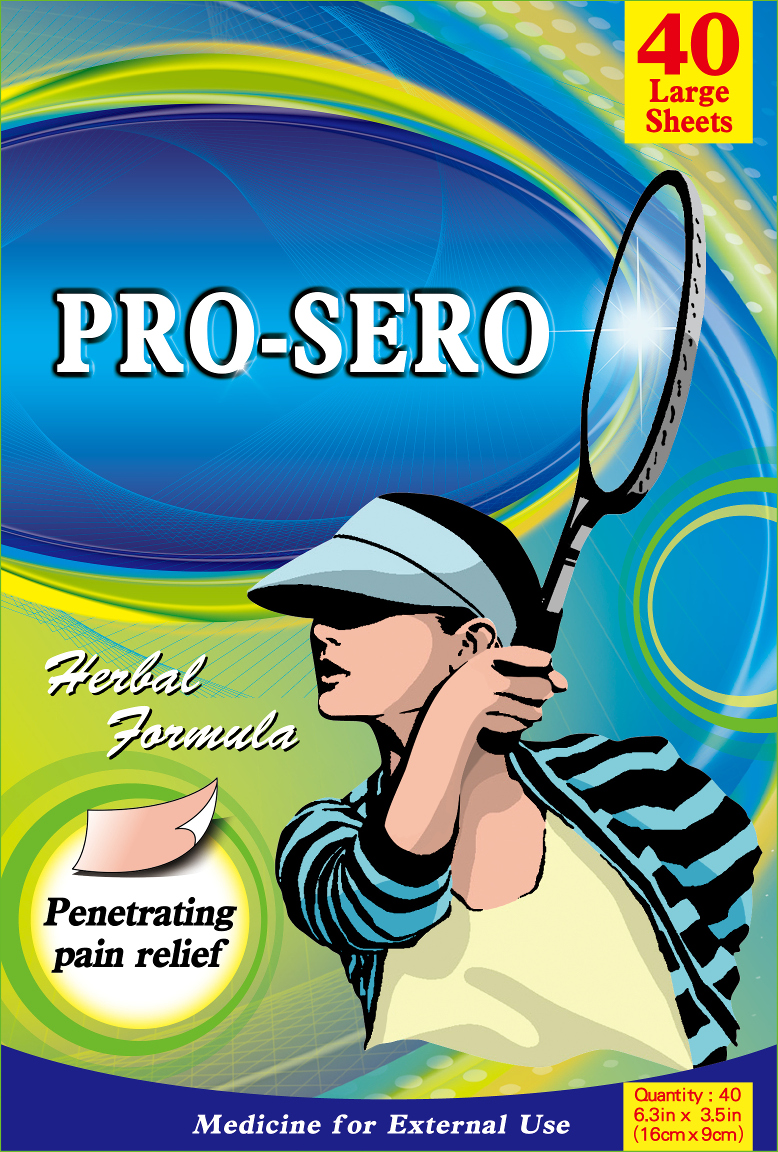 DRUG LABEL: Pro-Sero Pain Relief
NDC: 80846-100 | Form: PATCH
Manufacturer: Tieh Leh Biotech Co., Ltd.
Category: otc | Type: HUMAN OTC DRUG LABEL
Date: 20200924

ACTIVE INGREDIENTS: METHYL SALICYLATE 24 mg/1 1; MENTHOL 96 mg/1 1
INACTIVE INGREDIENTS: SESAME OIL; CLEMATIS CHINENSIS ROOT; FD&C YELLOW NO. 5; FRANKINCENSE; INDIGOTINDISULFONATE SODIUM; MYRRH; RICINUS COMMUNIS SEED; YELLOW WAX; MOMORDICA COCHINCHINENSIS SEED; PINUS MASSONIANA RESIN; ZINC OXIDE

Active ingredients

Menthol 4%

Methyl Salicylate 1%

Purpose

Topical analgesic

Uses

Temporarily relieves mild to moderate aches and pains of muscles and joints associated with:

- arthritis
- simple backache
- sprains
- strains
- bruises

Warnings

For external use only

Alergy alert:

If prone to allergic reaction from aspirin or salicylates, consult a doctor before use.

Do not use

- on the face or rashes
- on wounds or damaged skin
- if allergic to any ingredient of this product
- on a child under 12 years of age with arthritis-like conditions

Ask a doctor before use if

- you are allergic to topical products

When using this product

- wash hands after applying or removing patch
- avoid contact with eyes. If eye contact occurs, rinse thoroughly with water.

Stop use and ask a doctor if

- rash, itching or skin irritaion develops
- condition worsens
- symptoms last for more than 7 days
- symptoms clear up and occur again within a few days

If pregnant or breast-feeding

- ask a health professional before use

Keep our of reach of children. Package not child resistant.

If swallowed, get medical help or contact a Poison Control Center (1-800-222-1222) right away

Directions

Adults and children 12 years of age and over:

- clean and dry affected area
- remove patch from film and apply to affected area
- leave in place for up to 8 to 12 hours
- apply a new patch up to 3 times daily
- Children under 12 years of age: Consult a doctor

Other information

- store at 20 - 25 degrees Celsius (68-77 degrees Fahrenheit)
- avoid storing product in direct sunlight
- protect product from excessive moisture
- reseal unused patches in their pouch
- for some individuals, pain relief begins several hours after applying the patch

Inactive ingredients

Clematis Chinensis Root, FD&C Yellow No. 5, Frankincense, Indigotindisulfonate Sodium, Momordica Cochinchinensis Seed, Myrrh, Ricinus Communis Seed, Rosin, Sesame Oil, Yellow Wax, Zinc Oxide

Questions or comments?

Visit www.pro-sero.com